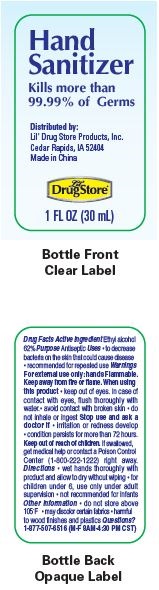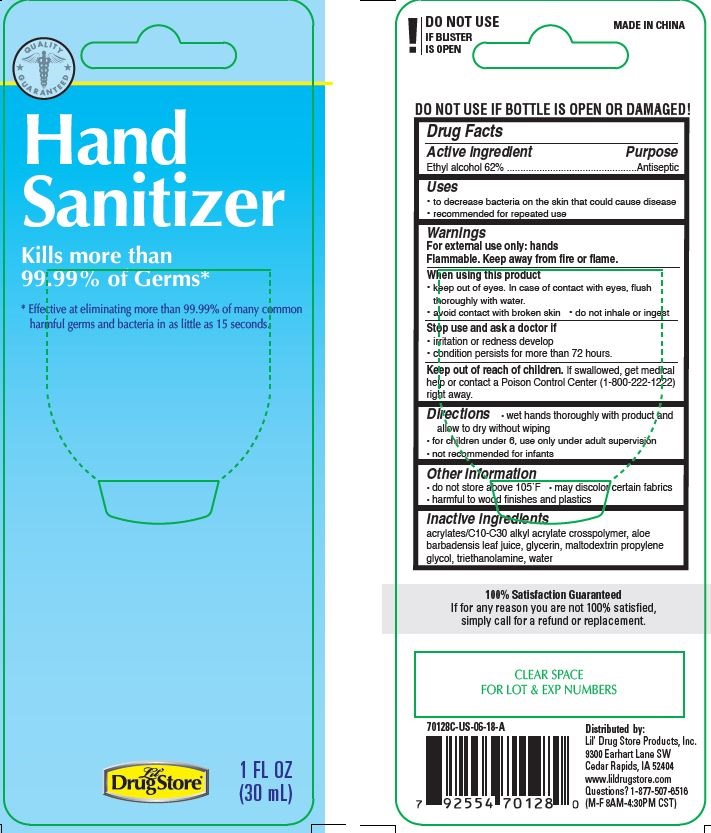 DRUG LABEL: Hand Sanitizer
NDC: 66715-7012 | Form: GEL
Manufacturer: Lil' Drug Store Products, Inc
Category: otc | Type: HUMAN OTC DRUG LABEL
Date: 20241231

ACTIVE INGREDIENTS: ALCOHOL 0.62 mL/1 mL
INACTIVE INGREDIENTS: WATER; TROLAMINE; GLYCERIN; PROPYLENE GLYCOL; CARBOMER INTERPOLYMER TYPE A (ALLYL SUCROSE CROSSLINKED); ISOPROPYL MYRISTATE; ISOPROPYL ALCOHOL; ALOE VERA LEAF; .ALPHA.-TOCOPHEROL

Lil' Drug Store® Hand Sanitizer

Drug Facts

Active ingredient

Ethyl alcohol 62% w/w

Purpose

Antiseptic

Use

- for handwashing to decrease bacteria on the skin

Warnings

Flammable, keep away from fire or flame.

For external use only.

Do not use

- in the eyes. In case of contact, rinse eyes thoroughly with water.

Stop use and ask a doctor if

- irritation and redness develop and persists for more than 72 hours.

Keep out of reach of children. If swallowed, get medical help or contact a Poison Control Center right away.

Directions

- wet hands thoroughly with product
- briskly rub hands together until dry
- supervise children in the use of this product

Other information

- store at room temperature 15° to 30°C (59° to 86°F)
- may discolor certain fabrics

Inactive ingredients

water, carbomer, fragrance, triethanolamine, glycerin, propylene glycol, isopropyl alcohol, isopropyl myristate, tocopheryl acetate, aloe vera extract

Questions or comments?

call toll-free 1-877-507-6516 (M-F 8AM-4:30PM CST)

Distributed by: Lil' Drug Store Products, Inc.
1201 Continental Place NE, Cedar Rapids, IA 52402

PRINCIPAL DISPLAY PANEL - 30 mL Bottle Blister Pack - Card & Bottle Label

QUALITY

GUARANTEED [caduceus]

Hand

Sanitizer

Kills more than

99.99% of Germs*

*Effective at eliminating more than 99.99% of many common

harmful germs and bacteria in as little as 15 seconds.

[Lil' Drug Store logo]

1 FL OZ

(30 mL)